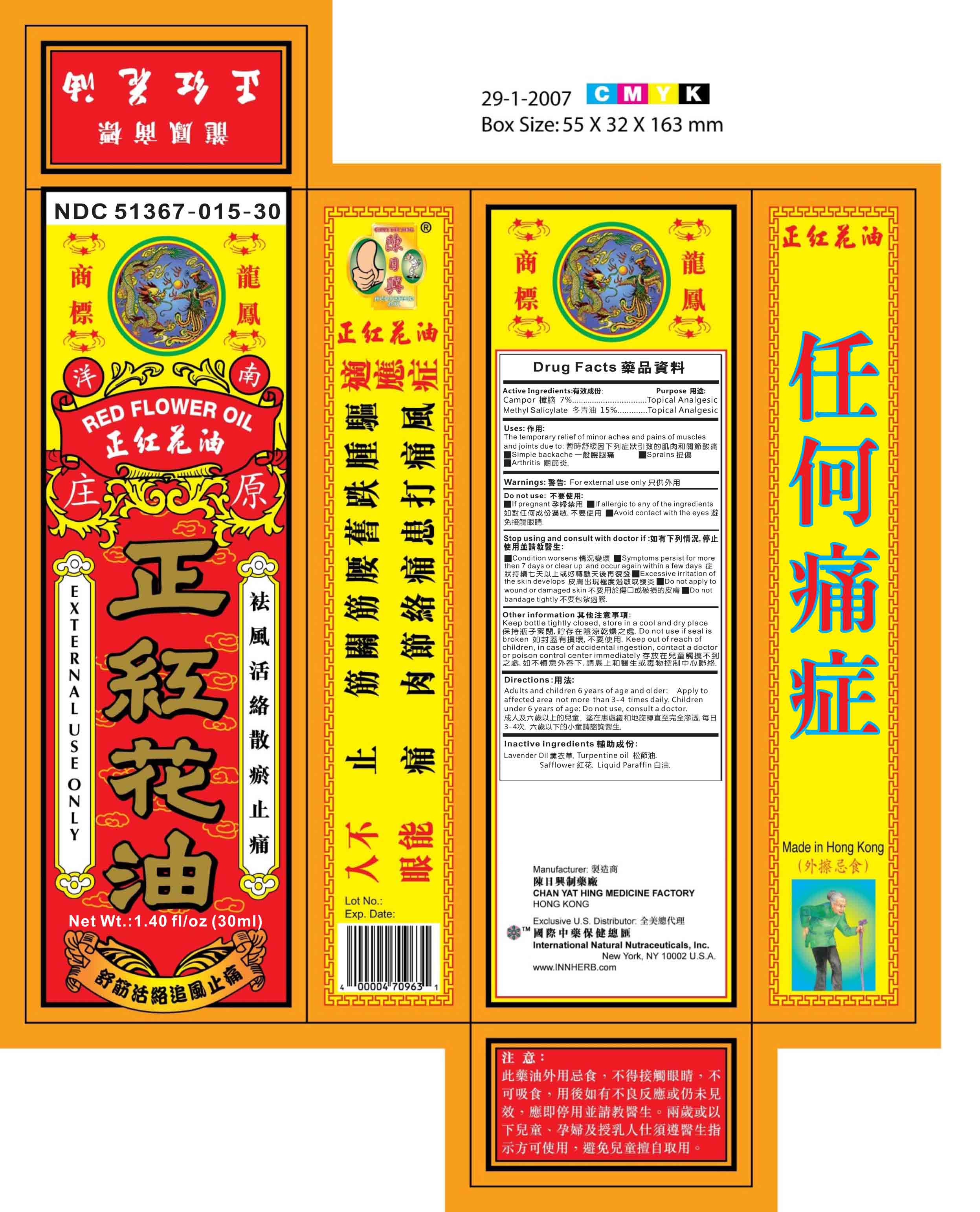 DRUG LABEL: Red Flower Oil
NDC: 51367-015 | Form: OIL
Manufacturer: International Nature Nutraceuticals
Category: otc | Type: HUMAN OTC DRUG LABEL
Date: 20131020

ACTIVE INGREDIENTS: CAMPHOR (NATURAL) 2.09 g/1 1; METHYL SALICYLATE 5.28 g/1 1
INACTIVE INGREDIENTS: LAVENDER OIL; TURPENTINE OIL; SAFFLOWER; PARAFFIN

Drug Facts

Active Ingredients

Camphor- 7%

Methyl Salicylate- 15%

Uses

The temporary relief of minor aches and pains of muscles

and joints due to: 暫時舒緩因下列症狀引致的肌肉和關節酸痛

Simple backache

Arthritis 關節炎.

Warnings:

For external use only

Do not use:

If pregnant 孕婦禁用 If allergic to any of the ingredients

如對任何成份過敏,不要使用 Avoid contact with the eyes 避

免接觸眼睛.

Stop using and consult with a doctor if:

Condition worsens 情況變壞 Symptoms persist for more

then 7 days or clear up and occur again within a few days 症

狀持續七天以上或好轉數天後再復發 Excessive irritation of

the skin develops 皮膚出現極度過敏或發炎 Do not apply to

wound or damaged skin 不要用於傷口或破損的皮膚 Do not

bandage tightly 不要包紮過緊.

Keep out of reach of children

In case of accidental ingestion, contact a doctor or poision control center immediately.

Directions

Adults and children 6 years of age and older: Apply to

affected area not more than 3~4 times daily. Children

under 6 years of age: Do not use, consult a doctor.

成人及六歲以上的兒童, 塗在患處緩和地旋轉直至完全滲透,每日

3-4次. 六歲以下的小童請諮詢醫生.

Other Information:

Keep bottle tightly closed, store in a cool and dry place

保持瓶子緊閉,貯存在陰涼乾燥之處.Do not use if seal is

broken 如封蓋有損壞,不要使用

Inactive Ingredients

Lavender Oil 薰衣草, Turpentine oil 松節油, Safflower 紅花, Liquid Paraffin 白油.